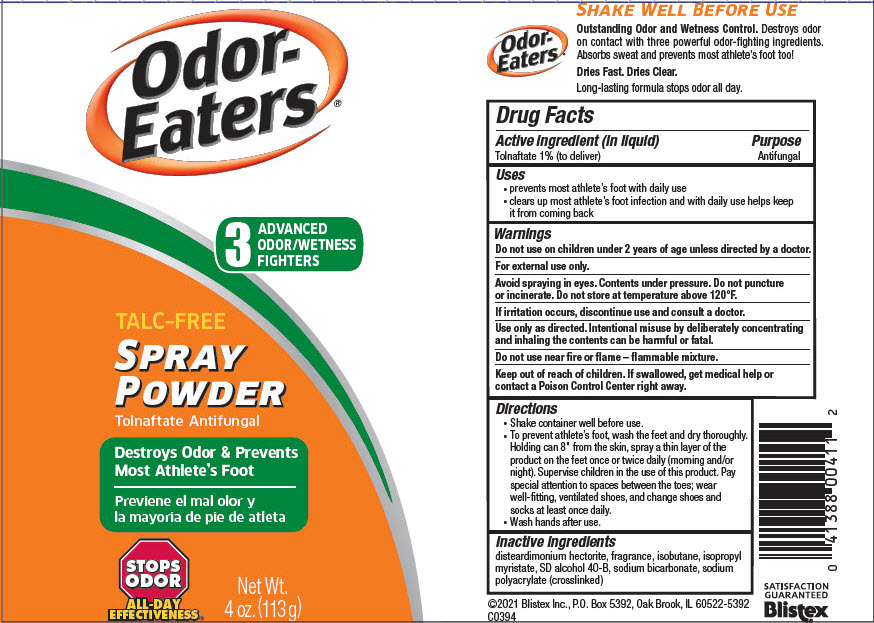 DRUG LABEL: Blistex 
NDC: 10157-4645 | Form: SPRAY
Manufacturer: Blistex Inc
Category: otc | Type: HUMAN OTC DRUG LABEL
Date: 20241212

ACTIVE INGREDIENTS: Tolnaftate 1 g/100 g
INACTIVE INGREDIENTS: ISOBUTANE; SODIUM BICARBONATE; ISOPROPYL MYRISTATE; DISTEARDIMONIUM HECTORITE

Blistex
Odor-Eaters® Spray Powder

Drug Facts

Active ingredient (in liquid)

Tolnaftate 1% (to deliver)

Purpose

Antifungal

Uses

- prevents most athlete's foot with daily use
- clears up most athlete's foot infection and with daily use helps keep it from coming back

Warnings

Do not use on children under 2 years of age unless directed by a doctor.

For external use only.

WHEN USING

Avoid spraying in eyes. Contents under pressure. Do not puncture or incinerate. Do not store at temperature above 120°F.

STOP USE

If irritation occurs, discontinue use and consult a doctor.

WHEN USING

Use only as directed. Intentional misuse by deliberately concentrating and inhaling the contents can be harmful or fatal.

Do not use near fire or flame – flammable mixture.

Keep out of reach of children. If swallowed, get medical help or contact a Poison Control Center right away.

Directions

- Shake container well before use.
- To prevent athlete's foot, wash the feet and dry thoroughly. Holding can 8" from the skin, spray a thin layer of the product on the feet once or twice daily (morning and/or night). Supervise children in the use of this product. Pay special attention to spaces between the toes; wear well-fitting, ventilated shoes, and change shoes and socks at least once daily.
- Wash hands after use.

Inactive ingredients

disteardimonium hectorite, fragrance, isobutane, isopropyl myristate, SD alcohol 40-B, sodium bicarbonate, sodium polyacrylate (crosslinked)

PRINCIPAL DISPLAY PANEL - 113 g Can Label

Odor-
Eaters®

3
ADVANCED
ODOR/WETNESS
FIGHTERS

TALC-FREE
SPRAY
POWDER
Tolnaftate Antifungal

Destroys Odor & Prevents
Most Athlete's Foot

STOPS
ODOR

ALL-DAY
EFFECTIVENESS®

Net Wt.
4 oz. (113 g)